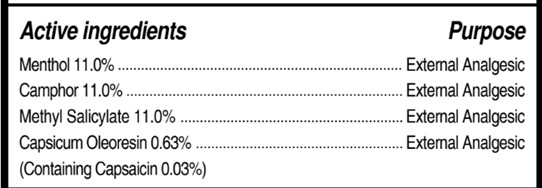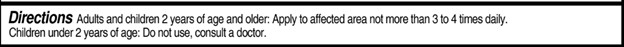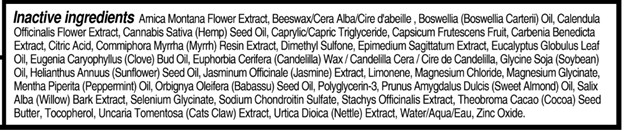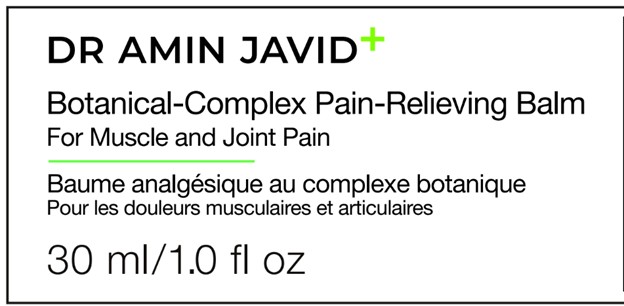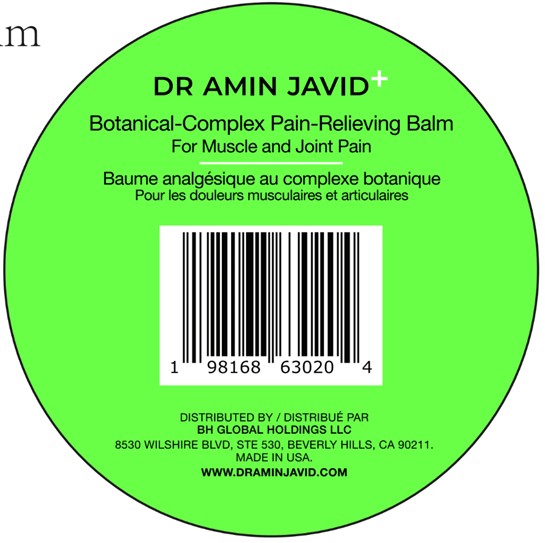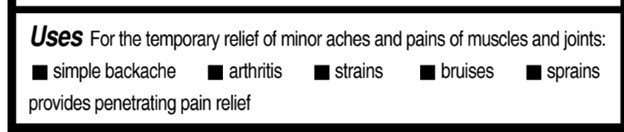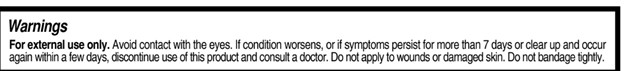 DRUG LABEL: DR AMIN JAVID Botanical-Complex Pain-Relieving Balm, 30 ml/1.0 fl oz
NDC: 84521-3001 | Form: CREAM
Manufacturer: BH GLOBAL HOLDINGS LLC
Category: otc | Type: HUMAN OTC DRUG LABEL
Date: 20251001

ACTIVE INGREDIENTS: CAMPHOR (SYNTHETIC) 11 g/100 g; LEVOMENTHOL 11 g/100 g; METHYL SALICYLATE 11 g/100 g; CAPSICUM OLEORESIN 0.03 g/100 g
INACTIVE INGREDIENTS: EPIMEDIUM SAGITTATUM WHOLE; SALIX ALBA BARK; UNCARIA TOMENTOSA WHOLE; ARNICA MONTANA FLOWER; MAGNESIUM GLYCINATE; BOSWELLIA CARTERII OIL; CAPRYLIC/CAPRIC TRIGLYCERIDE; PRUNUS AMYGDALUS DULCIS (SWEET ALMOND) OIL; JASMINUM OFFICINALE WHOLE; MAGNESIUM CHLORIDE; POLYGLYCERIN-3; TRIGLYCINE SELENATE; SOYBEAN OIL; PEPPERMINT OIL TERPENELESS; ORBIGNYA OLEIFERA SEED OIL; STACHYS OFFICINALIS; WATER; ZINC OXIDE; HELIANTHUS ANNUUS (SUNFLOWER) SEED OIL; THEOBROMA CACAO (COCOA) SEED BUTTER; URTICA DIOICA; LIMONENE, (+)-; CAPSICUM FRUTESCENS FRUIT; CENTAUREA BENEDICTA WHOLE; COMMIPHORA MYRRHA RESIN; EUCALYPTUS GLOBULUS LEAF OIL; TOCOPHEROL; CALENDULA OFFICINALIS FLOWER; CANNABIS SATIVA SEED OIL; CITRIC ACID; DIMETHYL SULFONE; EUGENIA CARYOPHYLLUS (CLOVE) BUD OIL; SODIUM CHONDROITIN SULFATE (PORCINE; 5500 MW); EUPHORBIA CERIFERA (CANDELILLA) WAX; BEESWAX

DR AMIN JAVID Botanical-Complex Pain-Relieving Balm